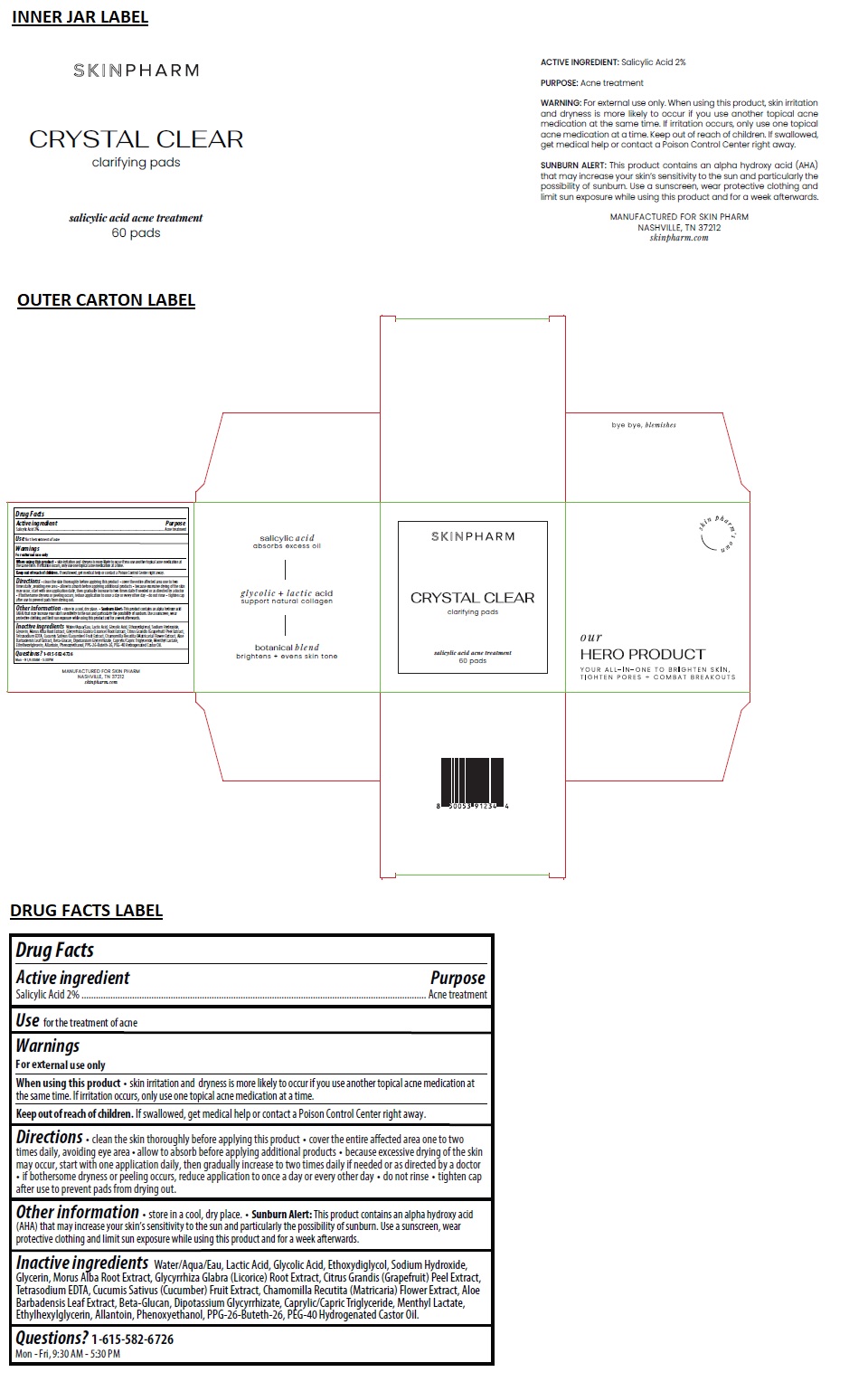 DRUG LABEL: Crystal Clear Acne Treatment Pads
NDC: 83316-001 | Form: PATCH
Manufacturer: Skin Pharm, LLC
Category: otc | Type: HUMAN OTC DRUG LABEL
Date: 20240522

ACTIVE INGREDIENTS: SALICYLIC ACID 2 g/100 mL
INACTIVE INGREDIENTS: WATER; LACTIC ACID, UNSPECIFIED FORM; GLYCOLIC ACID; DIETHYLENE GLYCOL MONOETHYL ETHER; SODIUM HYDROXIDE; GLYCERIN; MORUS ALBA ROOT; GLYCYRRHIZA GLABRA; CITRUS MAXIMA FRUIT RIND; EDETATE SODIUM; CUCUMBER; CHAMOMILE; ALOE VERA LEAF; YEAST .BETA.-D-GLUCAN; GLYCYRRHIZINATE DIPOTASSIUM; MEDIUM-CHAIN TRIGLYCERIDES; MENTHYL LACTATE, (-)-; ETHYLHEXYLGLYCERIN; ALLANTOIN; PHENOXYETHANOL; PPG-26-BUTETH-26; POLYOXYL 40 HYDROGENATED CASTOR OIL

CRYSTAL CLEAR Salicylic Acid Acne Treatment Pads

Active ingredient

Salicylic Acid 2%

Purpose

Acne treatment

Use

for the treatment of acne

Warnings

For external use only

When using this product • skin irritation and dryness is more likely to occur if you use another topical acne medication at the same time. If irritation occurs, only use one topical acne medication at a time.

Keep out of reach of children. If swallowed, get medical help or contact a Poison Control Center right away.

Directions

• clean the skin thoroughly before applying this product • cover the entire affected area one to two times daily, avoiding eye area • allow to absorb before applying additional products • because excessive drying of the skin may occur, start with one application daily, then gradually increase to two times daily if needed or as directed by a doctor • if bothersome dryness or peeling occurs, reduce application to once a day or every other day • do not rinse • tighten cap after use to prevent pads from drying out.

Other information

• store in a cool, dry place. • Sunburn Alert: This product contains an alpha hydroxy acid (AHA) that may increase your skin’s sensitivity to the sun and particularly the possibility of sunburn. Use a sunscreen, wear protective clothing and limit sun exposure while using this product and for a week afterwards.

Inactive ingredients

Water/Aqua/Eau, Lactic Acid, Glycolic Acid, Ethoxydiglycol, Sodium Hydroxide, Glycerin, Morus Alba Root Extract, Glycyrrhiza Glabra (Licorice) Root Extract, Citrus Grandis (Grapefruit) Peel Extract, Tetrasodium EDTA, Cucumis Sativus (Cucumber) Fruit Extract, Chamomilla Recutita (Matricaria) Flower Extract, Aloe Barbadensis Leaf Extract, Beta-Glucan, Dipotassium Glycyrrhizate, Caprylic/Capric Triglyceride, Menthyl Lactate, Ethylhexylglycerin, Allantoin, Phenoxyethanol, PPG-26-Buteth-26, PEG-40 Hydrogenated Castor Oil.

Questions?

+1-615-582-6726
Mon - Fri, 9:30 AM - 5:30 PM

skin pharm's own

our

HERO PRODUCT

YOU ALL-IN-ONE TO BRIGHTEN SKIN, TIGHTEN PORES + COMBAT BREAKOUTS

salicylic acid
absorbs excess oil

glycolic + lactic acid
support natural collagen

botanical blend
brightens + evens skin tone

bye bye, blemishes

MANUFACTURED FOR SKIN PHARM
NASHVILLE, TN 37212
skinpharm.com